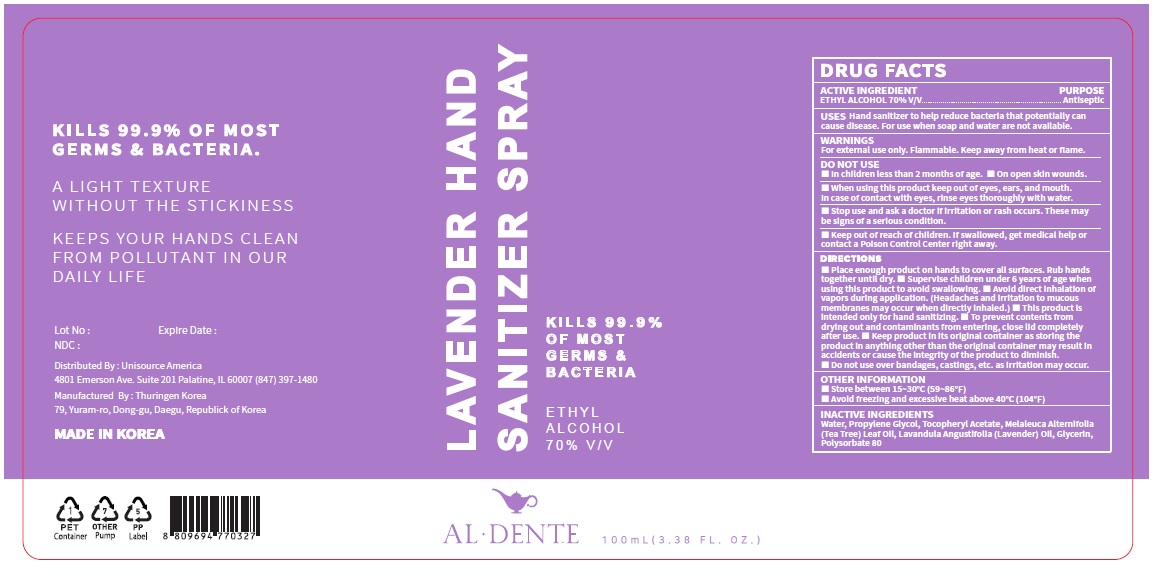 DRUG LABEL: LAVENDER HAND SANITIZER
NDC: 74864-0001 | Form: SPRAY
Manufacturer: THURINGEN KOREA Co., Ltd.
Category: otc | Type: HUMAN OTC DRUG LABEL
Date: 20201203

ACTIVE INGREDIENTS: ALCOHOL 70 mL/100 mL
INACTIVE INGREDIENTS: WATER; PROPYLENE GLYCOL; .ALPHA.-TOCOPHEROL ACETATE; TEA TREE OIL; LAVENDER OIL; GLYCERIN; POLYSORBATE 80

Lavender Hand Sanitizer Spary: 74864-0001